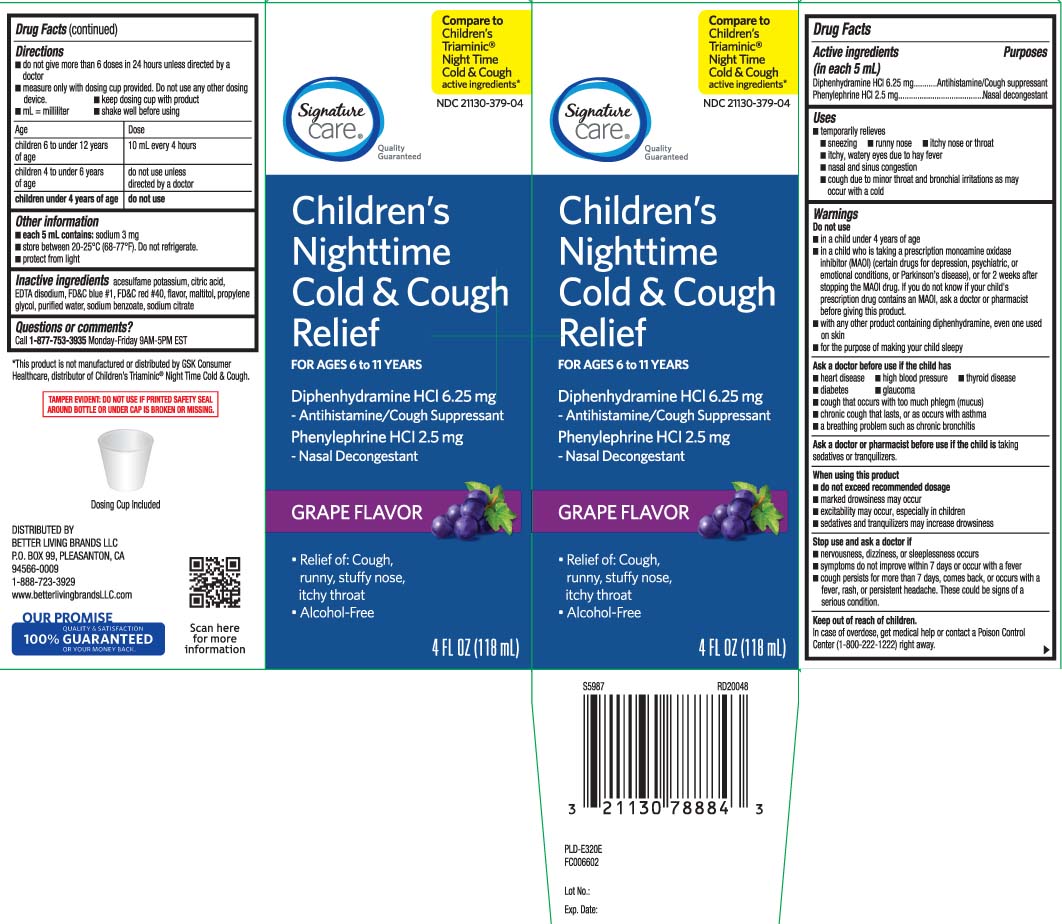 DRUG LABEL: Childrens Cold and Cough
NDC: 21130-379 | Form: LIQUID
Manufacturer: Safeway, Inc.
Category: otc | Type: HUMAN OTC DRUG LABEL
Date: 20240515

ACTIVE INGREDIENTS: DIPHENHYDRAMINE HYDROCHLORIDE 6.25 mg/5 mL; PHENYLEPHRINE HYDROCHLORIDE 2.5 mg/5 mL
INACTIVE INGREDIENTS: ACESULFAME POTASSIUM; SODIUM BENZOATE; ANHYDROUS CITRIC ACID; EDETATE DISODIUM; MALTITOL; PROPYLENE GLYCOL; WATER; FD&C RED NO. 40; TRISODIUM CITRATE DIHYDRATE; FD&C BLUE NO. 1

Drug Facts

Active ingredients (in each 5 mL)

Diphenhydramine HCl 6.25 mg

Phenylephrine HCl 2.5 mg

Purposes

Antihistamine/Cough suppressant

Nasal decongestant

Uses

- temporarily relieves
  - sneezing
  - runny nose
  - itchy nose or throat
  - itchy, watery eyes due to hay fever
  - nasal and sinus congestion
  - cough due to minor throat and bronchial irritations as may occur with a cold

Warnings

Do not use

- in a child under 4 years of age
- in a child who is taking a prescription monoamine oxidase inhibitor (MAOI) (certain drugs for depression, psychiatric or emotional conditions, or Parkinson’s disease), or for 2 weeks after stopping the MAOI drug. If you do not know if your child's prescription drug contains an MAOI, ask a doctor or pharmacist before giving this product.
- with any other product containing diphenhydramine, even one used on skin
- for the purpose of making your child sleepy

Ask a doctor before use if the child has

- heart disease
- high blood pressure
- thyroid disease
- diabetes
- glaucoma
- cough that occurs with too much phlegm (mucus)
- chronic cough that lasts, or as occurs with asthma
- a breathing problem such as chronic bronchitis

Ask a doctor or pharmacist before use if the child is

taking sedative or tranquilizers.

When using this product,

- do not exceed recommended dosage
- marked drowsiness may occur
- excitability may occur, especially in children
- sedatives and tranquilizers may increase drowsiness

Stop use and ask a doctor if

- nervousness, dizziness or sleeplessness occurs
- symptoms do not improve within 7 days or occur with a fever
- cough persists for more than 7 days, comes back or occurs with fever, rash or persistent headache.

These could be signs of a serious condition.

Keep out of reach of children.

In case of overdose, get medical help or contact a Poison Control Center (1-800-222-1222) right away.

Directions

- Do not give more than 6 doses in 24 hours unless directed by a doctor.
- measure only with dosing cup provided Do not use any other dosing device
- keep dosing cup with product
- mL=mililiter
- shake well before using

Age | Dose
children 6 to under 12 years | 10 mL every 4 hours
children 4 to under 6 years | do not use unless directed by a doctor
children under 4 years of age | do not use

Other Information

- each 5 mL contains: sodium 3 mg
- store between 20-25ºC (68-77ºF). Do not refrigerate.
- protect from light

Inactive ingredients

acesulfame potassium, anhydrous citric acid, EDTA disodium, FD&C blue #1, FD&C red #40, flavor, maltitol, propylene glycol, purified water, sodium benzoate, trisodium citrate dihydrate

Questions or comments?

Call 1-888-723-3929 Monday-Friday 7AM-6PM PST

Principal Display Panel

Compare to Children's Triaminic® NightTime Cold & Cough active ingredients*

Childrens's Nighttime

Cold & Cough Relief

FOR AGES 6-11 YEARS

Diphenhydramine HCl 6.25 mg - Antihistamine/Cough Suppressant

Phenylephrine HCl 2.5 mg - Nasal Decongestant

GRAPE FLAVOR

- Relief of: Cough, runny, stuffy nose itchy throat
- Alcohol-Free

FL OZ (mL)

TAMPER EVIDENT: DO NOT USE IF PRINTED SAFETY SEAL AROUND BOTTLE OR UNDER CAP IS BROKEN OR MISSING.

*This product is not manufactured or distributed by GSK Consumer Healthcare, distributors of Children's Triaminic® Night Time Cold & Cough.

DISTRIBUTED BY

BETTER LIVING BRANDS LLC

P.O. BOX 99, PLEASANTON, CA 94566-0009

www.betterlivingbrandsLLC.com

Package Label

SIGNATURE CARE Children's Nighttime Cold and Cough Relief Grape Flavor